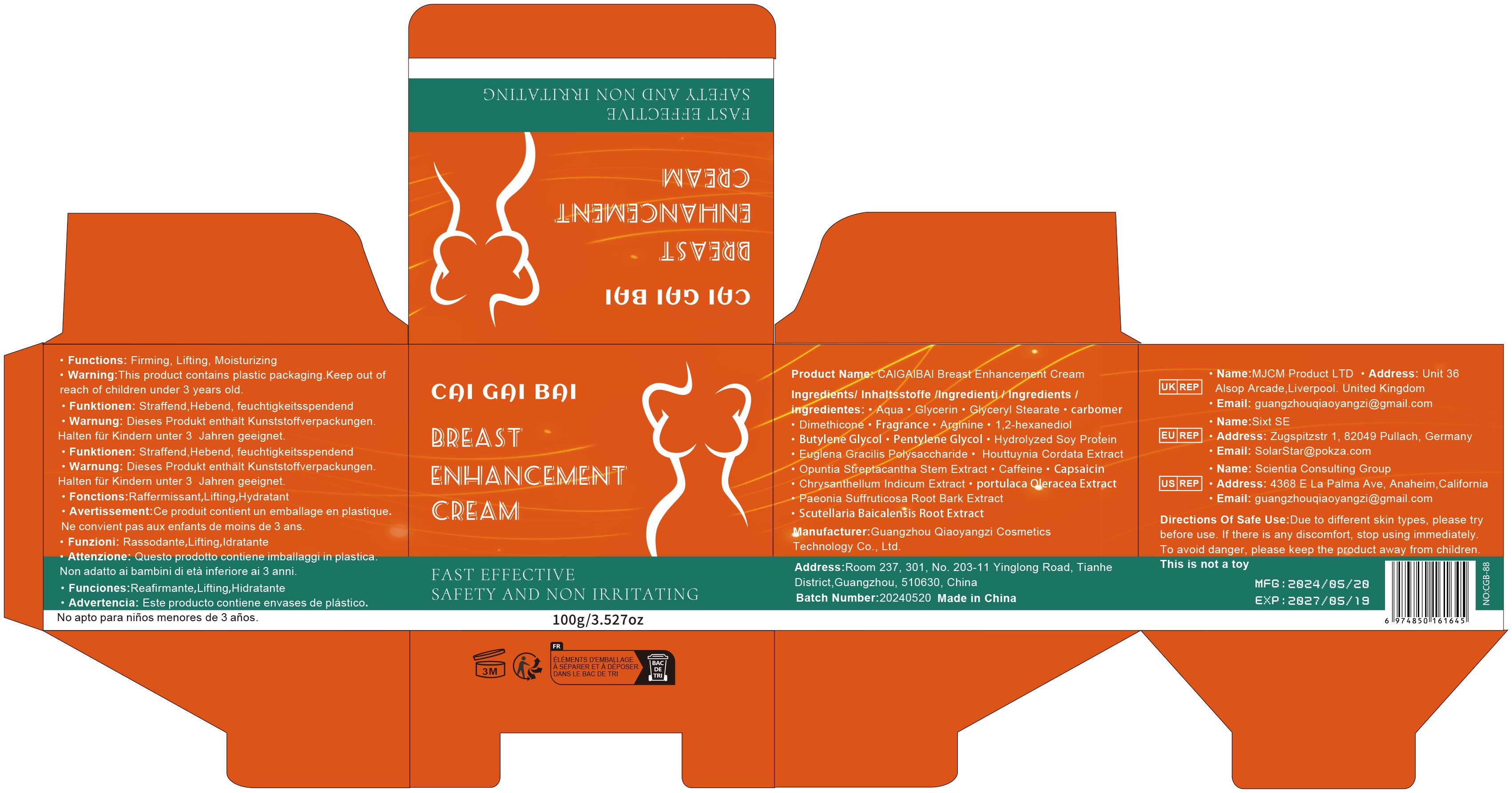 DRUG LABEL: Breast Enhancement Cream
NDC: 84751-088 | Form: EMULSION
Manufacturer: Guangzhou Qiaoyangzi Cosmetics Technology Co Ltd
Category: otc | Type: HUMAN OTC DRUG LABEL
Date: 20241030

ACTIVE INGREDIENTS: PURSLANE 0.25 g/100 g; OPUNTIA STREPTACANTHA STEM 0.55 g/100 g; SCUTELLARIA BAICALENSIS ROOT 0.2 g/100 g; CHRYSANTHELLUM INDICUM TOP 0.35 g/100 g; HYDROLYZED SOY PROTEIN (ENZYMATIC; 2000 MW) 3.5 g/100 g; EUGLENA GRACILIS 2.5 g/100 g; HOUTTUYNIA CORDATA EXTRACT 0.35 g/100 g; CAFFEINE 0.3 g/100 g; CAPSAICIN 0.1 g/100 g; PAEONIA LACTIFLORA ROOT 0.2 g/100 g
INACTIVE INGREDIENTS: GLYCERIN 5 g/100 g; AQUA 78.68 g/100 g

Active ingredients

HYDROLYZED SOY PROTEIN 3.50%
EUGLENA GRACILIS 2.50%
OPUNTIA STREPTACANTHA STEM EXTRACT 0.55%
HOUTTUYNIA CORDATA EXTRACT 0.35%
CHRYSANTHELLUM INDICUM EXTRACT 0.35%
CAFFEINE 0.30%
PORTULACA OLERACEA EXTRACT 0.25%
Paeonia Lactiflora Root Extract 0.20%
SCUTELLARIA BAICALENSIS ROOT EXTRACT 0.20%
CAPSAICIN 0.10%

INACTIVE INGREDIENT SECTION

AQUA 78.68%
GLYCERIN 5.00%
GLYCERYL STEARATE 3.00%
CARBOMER 3.50%
DIMETHICONE 0.55%
FRAGRANCE 0.50%
ARGININE 0.35%
1,2-HEXANEDIOL 0.05%
BUTYLENE GLYCOL 0.04%
PENTYLENE GLYCOL 0.03%

Purpose

Used to improve the firmness and elasticity of breast skin, helping to uplift and shape, promoting smoothness and softness, and reducing the appearance of skin sagging.

Uses

Indications: Used for firming and lifting breast skin, enhancing its elasticity and smoothness; suitable for women looking to improve the appearance of their breasts.
Usage: Apply an appropriate amount of the product evenly to the breast area, gently massage until fully absorbed, and use 1-2 times daily.

Warnings

For external use only. Avoid contact with eyes. In case of accidental contact, rinse thoroughly with plenty of water.
Pregnant or nursing women and individuals with a history of skin allergies should consult a physician before use.
Discontinue use and consult a physician if redness, itching, or other discomfort occurs.
Keep out of reach of children.

Stop use

Discontinue use immediately if redness, itching, burning, or other discomfort occurs, and consult a physician.
If symptoms persist or worsen, seek medical attention promptly.

Do not use

Do not use if you are allergic to any ingredient.
This product is not intended for use on broken, inflamed, or diseased skin.
Not suitable for children.

Keep out of reach of children!

This product should be stored out of the reach of children. In case of accidental ingestion, seek medical help immediately or contact a poison control center.

Precautions for Use

When Using:
Avoid contact with eyes. In case of accidental contact, rinse thoroughly with plenty of water.
Do not apply this product on wounds or broken skin during use.
Monitor for skin reactions; discontinue use immediately if discomfort occurs.

Instructions for Use

Clean the breast area and ensure the skin is dry.
Take an appropriate amount of the product (about the size of a coin) and apply evenly to the breast area.
Gently massage in a circular motion until fully absorbed.
Use 1-2 times daily, once in the morning and once in the evening for best results.

DOSAGE & ADMINISTRATION SECTION

Dosage & Administration:
Use an appropriate amount of the product (about the size of a coin) each time.
It is recommended to use 1-2 times daily, once in the morning and once in the evening.
Massage until fully absorbed for optimal results.